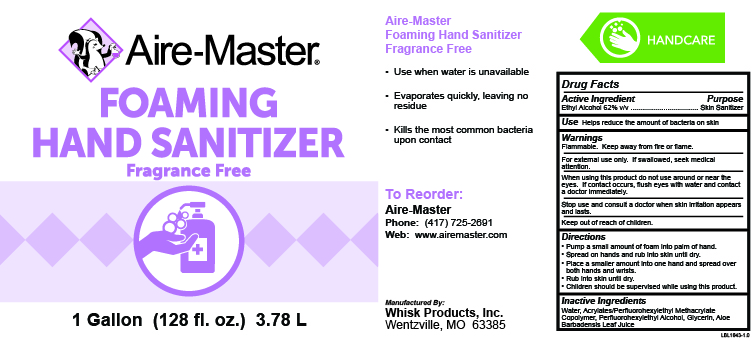 DRUG LABEL: Aire-Master Foaming Hand Sanitizer Fragrance Free
NDC: 65585-524 | Form: SOLUTION
Manufacturer: Whisk Products, Inc.
Category: otc | Type: HUMAN OTC DRUG LABEL
Date: 20231207

ACTIVE INGREDIENTS: ALCOHOL 620 mL/1 L
INACTIVE INGREDIENTS: BUTYL ACRYLATE/METHYL METHACRYLATE/PERFLUOROHEXYLETHYL METHACRYLATE COPOLYMER (SALUS AF); 2-(PERFLUOROHEXYL)ETHANOL; GLYCERIN; ALOE VERA LEAF

Aire-Master Foaming Hand Sanitizer Fragrance Free

Active Ingredient

Ethyl Alcohol 62% v/v

Purpose

Skin Sanitizer

Use

Helps reduce the amount of bacteria on skin

Warnings

Flammable. Keep away from fire or flame.

For external use only. If swallowed seek medical attention.

When using this product do not use around or near the eyes. If contact occurs, flush eyes with water and contact a doctor immediately.

Stop use and consult a doctor when skin irritation appears and lasts.

Keep out of reach of children.

Directions

- Pump a small amount of foam into palm of hand.
- Spread on hands and rub into skin until dry.
- Place a smaller amount into one hand and spread over both hands and wrists.
- Rub into skin until dry.
- Children should be supervised while using this product.

Inactive Ingredients

Water, Acrylates/Perfluorohexylethyl Methacrylate Copolymer, Perfluorohexylethyl Alcohol, Glycerin, Aloe Barbadensis Leaf Juice